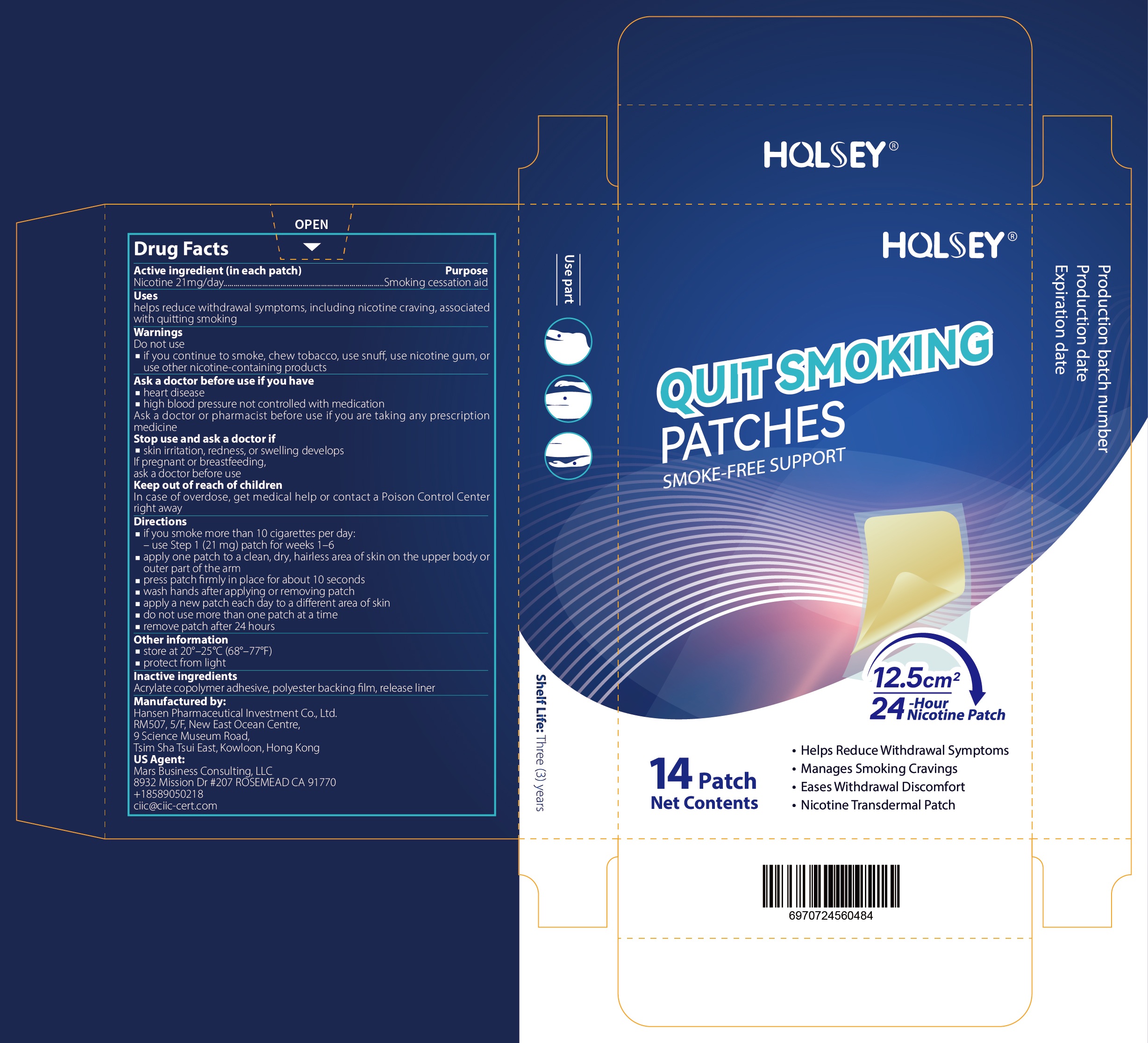 DRUG LABEL: HQLSEY QUIT SMOKING PATCHES
NDC: 87405-001 | Form: PATCH
Manufacturer: Hansen Pharmaceutical Investment Co., Limited
Category: otc | Type: HUMAN OTC DRUG LABEL
Date: 20260225

ACTIVE INGREDIENTS: NICOTINE 21 mg/100 1
INACTIVE INGREDIENTS: ACRYLIC ACID; POWDERED CELLULOSE; POLYESTER-7

87405-001

Active Ingredient

Nicotine 21 mg/day

Purpose

Smoking cessation aid

Use

helps reduce withdrawal symptoms, including nicotine craving, associatedwith quitting smoking

Warnings

if you continue to smoke, chew tobacco, use snuff, use nicotine gum, or use other nicotine-containing products

Do not use

if you continue to smoke, chew tobacco, use snuff, use nicotine gum, or use other nicotine-containing products

Stop Use

skin irritation, redness, or swelling develops

Ask Doctor

If pregnant or breastfeeding,ask a doctor before use

Keep Out Of Reach Of Children

In case of overdose, get medical help or contact a Poison Control Center right away

Directions

·if you smoke more than 10 cigarettes per day:
-use Step 1 (21 mg) patch for weeks 1-6
·apply one patch to a clean, dry, hairless area of skin on the upper body or outer part of the arm
·press patch frmly in place for about 10 seconds
·wash hands after applying or removing patch
·apply a new patch each day to a different area of skin
·do not use more than one patch at a time
·remove patch after 24 hours

Inactive ingredients

Acrylate copolymer adhesive, polyester backing film, release liner

Questions

For more information, please contact Hansen Pharmaceutical Investment Co. Ltd.
Address: RM507, 5/F, New East Ocean Centre,9 Science Museum Road,Tsim Sha Tsui East, Kowloon, Hong Kong